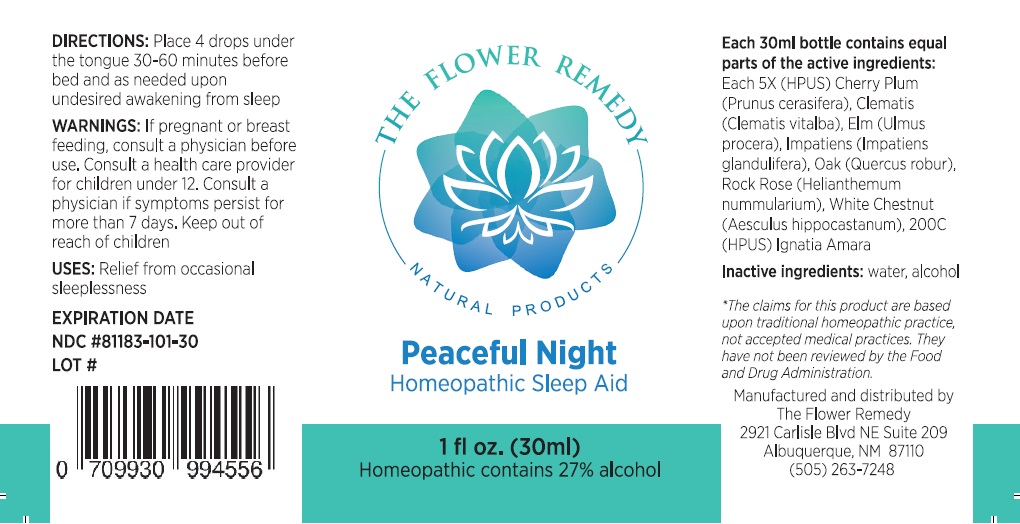 DRUG LABEL: THE FLOWER REMEDY Peaceful Night
NDC: 81183-101 | Form: LIQUID
Manufacturer: The Flower Remedy
Category: homeopathic | Type: HUMAN OTC DRUG LABEL
Date: 20251203

ACTIVE INGREDIENTS: PRUNUS CERASIFERA FLOWER 5 [hp_X]/30 mL; CLEMATIS VITALBA FLOWER 5 [hp_X]/30 mL; ULMUS MINOR FLOWERING TWIG 5 [hp_X]/30 mL; IMPATIENS GLANDULIFERA FLOWER 5 [hp_X]/30 mL; QUERCUS ROBUR FLOWER 5 [hp_X]/30 mL; HELIANTHEMUM NUMMULARIUM FLOWER 5 [hp_X]/30 mL; AESCULUS HIPPOCASTANUM FLOWER 5 [hp_X]/30 mL; STRYCHNOS IGNATII SEED 200 [hp_C]/30 mL
INACTIVE INGREDIENTS: WATER; ALCOHOL

THE FLOWER REMEDY NATURAL PRODUCTS Peaceful Night

Active Ingredients:

Each 30ml bottle contains equal parts of the active ingredients:
Each 5X (HPUS) Cherry Plum (Prunus cerasifera), Clematis (Clematis vitalba), Elm (Ulmus procera), Impatiens (Impatiens glandulifera), Oak (Quercus robur), Rock Rose (Helianthemum nummularium), White Chestnut (Aesculus hippocastanum), 200C (HPUS) Ignatia Amara

Purpose:

Sleep Aid

USES:

Relief from occasional sleeplessness

DIRECTIONS:

Place 4 drops under the tongue 30-60 minutes before bed and as needed upon undesired awakening from sleep

WARNINGS:

If pregnant or breast feeding, consult a physician before use. Consult a health care provider for children under 12. Consult a physician if symptoms persist for more than 7 days.

Keep out of reach of children.

Inactive ingredients:

water, alcohol

THE FLOWER REMEDY
NATURAL PRODUCTS

Homeopathic Sleep Aid

Homeopathic contains 27% alcohol

*The claims for this product are based upon traditional homeopathic practice, not accepted medical practices. They have not been reviewed by the Food and Drug Administration.

Manufactured and distributed by
The Flower Remedy
2921 Carlisle Blvd NE Suite 209
Albuquerque, NM 87110
(505) 263-7248